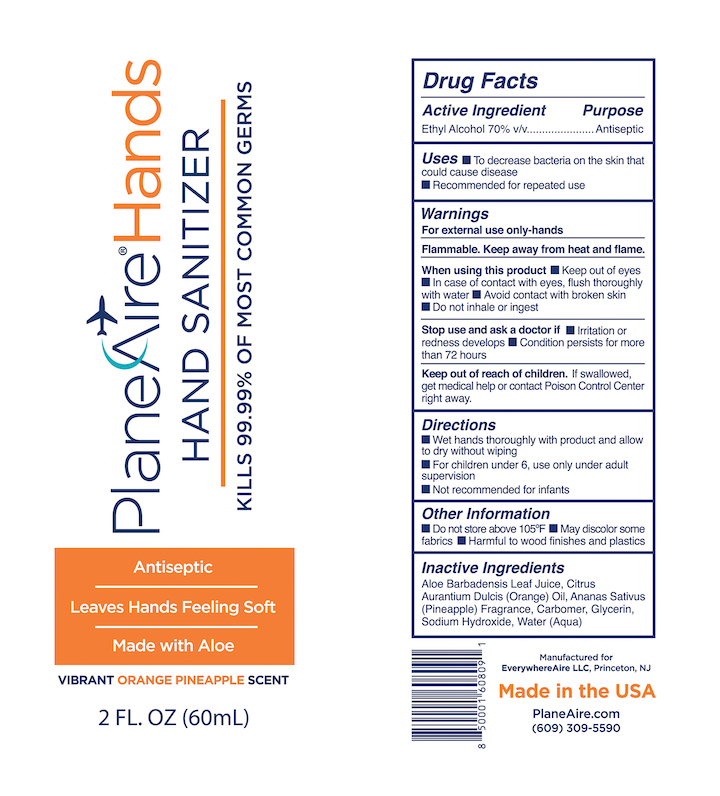 DRUG LABEL: PlaneAire Hands Hand Sanitizer
NDC: 80335-101 | Form: GEL
Manufacturer: EverywhereAire LLC
Category: otc | Type: HUMAN OTC DRUG LABEL
Date: 20211007

ACTIVE INGREDIENTS: ALCOHOL 70 mL/100 mL
INACTIVE INGREDIENTS: SODIUM HYDROXIDE; ALOE VERA LEAF POLYSACCHARIDES; CARBOMER 980; PINEAPPLE; ORANGE OIL; WATER; GLYCERIN

PlaneAireHands gel Orange-Pineapple

Active Ingredient(s)

Alcohol 70% v/v. Purpose: Antiseptic

Purpose

Antiseptic

Use

To decrease bacteria on skin that could cause disease. Recommended for repeated use.

Warnings

For external use only-hands. Flammable. Keep away from heat or flame

Do not use

- Not recommended for infants
- on open skin wounds

When using this product keep out of eyes. In case of contact with eyes, flush thoroughly with water.
Avoid contact with broken skin. Do not inhale or ingest.

Stop use and ask a doctor if irritation or rash develops. Condition persists for more than 72 hours.

Keep out of reach of children. If swallowed, get medical help or contact a Poison Control Center right away.

Directions

- Wet hands thoroughly with product and allow to dry without wiping
- For children under 6 , use only under adult supervision
- Not recommended for infants

Other information

- Do not store above 105F
- May discolor some fabrics
- Harmful to wood finishes and plastics

Inactive ingredients

aloe, carbomer, glycerin, sodium hydroxide, orange, pineapple, purified water

Uses

INDICATIONS

To decrease bacteria on the skin that could cause disease. Recommended for repeated use.

DIRECTIONS

Wet hands thoroughly with product and allow to dry without wiping
For children under 6 , use only under adult supervision
Not recommended for infants